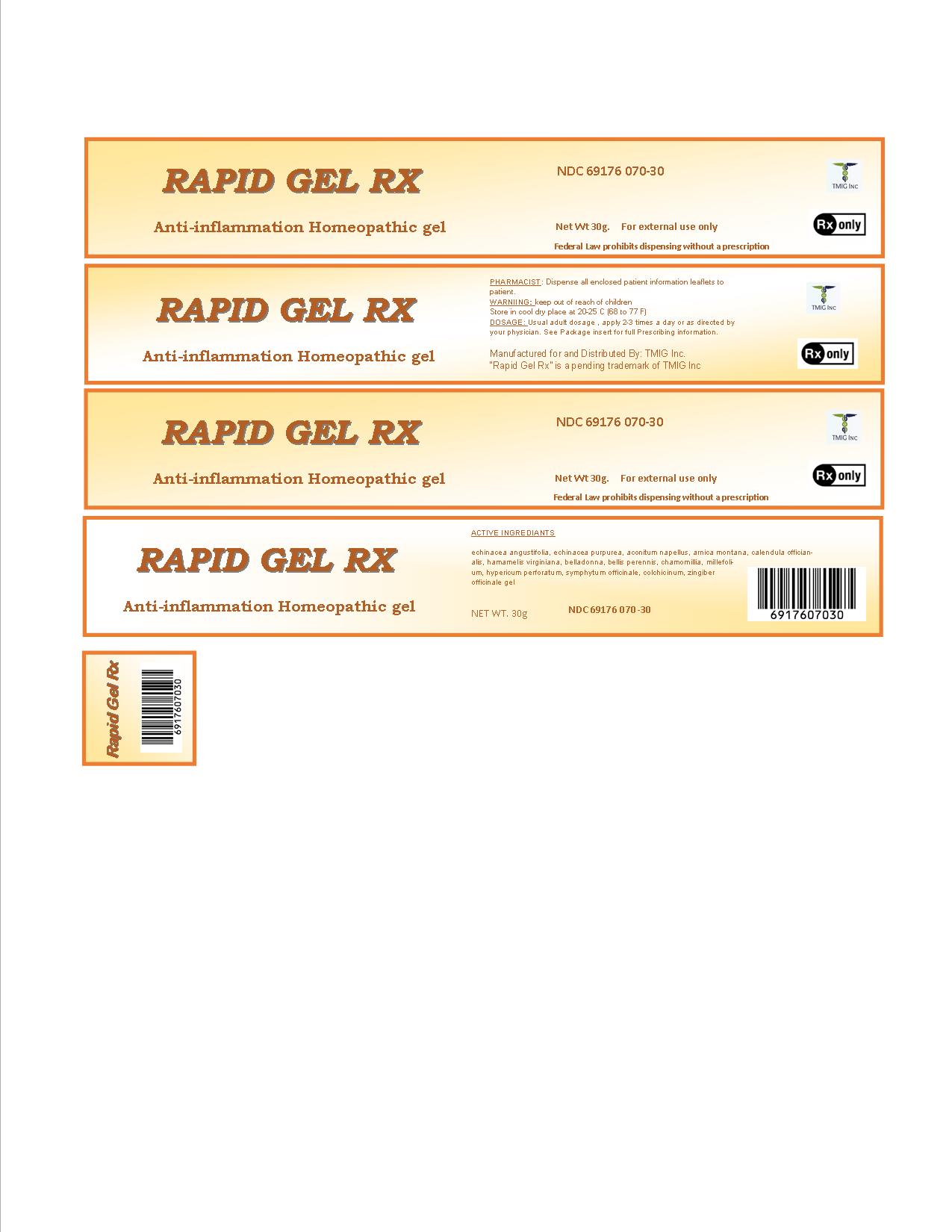 DRUG LABEL: Rapid Gel Rx
NDC: 69176-070 | Form: GEL
Manufacturer: TMIG Inc
Category: homeopathic | Type: HUMAN PRESCRIPTION DRUG LABEL
Date: 20160511

ACTIVE INGREDIENTS: ECHINACEA ANGUSTIFOLIA 1 [hp_X]/30 mL; ECHINACEA PURPUREA 1 [hp_X]/30 mL; ACONITUM NAPELLUS 3 [hp_X]/30 mL; ARNICA MONTANA 1 [hp_X]/30 mL; CALENDULA OFFICINALIS FLOWERING TOP 1 [hp_X]/30 mL; HAMAMELIS VIRGINIANA ROOT BARK/STEM BARK 1 [hp_X]/30 mL; ATROPA BELLADONNA 3 [hp_X]/30 mL; BELLIS PERENNIS 1 [hp_X]/30 mL; CHAMOMILE 1 [hp_X]/30 mL; ACHILLEA MILLEFOLIUM 1 [hp_X]/30 mL; HYPERICUM OIL 1 [hp_X]/30 mL; COMFREY ROOT 3 [hp_X]/30 mL; COLCHICINE 3 [hp_X]/30 mL; GINGER 1 [hp_X]/30 mL
INACTIVE INGREDIENTS: WATER; ISOPROPYL MYRISTATE; LECITHIN, SOYBEAN; UREA; DOCUSATE SODIUM; SODIUM HYDROXIDE

Rapid Gel Rx
TOPICAL ANTI-INFLAMATORY HOMEOPATHIC ANALGESIC

DESCRIPTION

Rapid Gel Rx is a homeopathic topical analgesic gel that contains the ingredients listed below.Homeopathic ingredients have been used since the inception of this science and remain as an effective method of treating select conditions. It is a white colored odorless gel for use externally to control inflammation and reduce pain.

It contains the following active ingredients:

Aconitum Napellus 3X, Arnica Montana 3X, Belladonna 3X, Bellis Perennis 1X, Calendula Officinalis 1X, Colchicinum 3X, Chamomilla 1X, Echinacea Angustifolia 1X, Echinacea Purpurea 1X, Hamamelis Virginiana 1X, Hypericum Perforatum 1X, Millefolium 1X, Symphytum Officinale 3X, Zingiber Officinale 1X.

It also contains the following inactive ingredients:

Purified water, Urea, Isopropyl myristate, Lecithin, Docusate sodium, Sodium hydroxide.

CLINICAL PHARMACOLOGY

The exact pharmacology by which Rapid Gel RX works to control aches and pains associated with arthritis or trauma (such as sprains, strains, dislocations, repetitive/overuse injuries, traumatic edema, post-surgical edema, hematoma, general swelling of joints and soft tissues) to such areas as hands, wrist, elbow, shoulder, neck, back, knees, ankles, feet and toes is unknown. It is theorized that, according to traditional homeopathy, the following ingredients contribute in the following ways:

Ingredients | Common Name | Indications
Aconitum Napellus | Monk’s-hood | Neuralgia, rheumatism,; hemostasis, analgesia
Arnica Montana | Mountain arnica | Stimulates healing of injured; tissues, wounds, contusions,; hematomas, neuralgia, myalgia,; analgesia
Belladonna | Deadly nightshade | Inflammation locally
Bellis Perennis | Daisy | Dislocations, bruising,; reducing edema
Calendula Officinalis | Calendula | Analgesia, inflammation
Colchicinum | Colchicine | Inflammation and gout
Chamomilla | Chamomile | Inflammation, promotes; healing of tissues
Echinacea Angustifolia | Narrow leaf cone flower | Inflammation and inhibits; hyaluronidase
Echinacea Purpurea | Purple cone flower | Stimulates fibroblasts,; inflammation
Hamamelis Virginiana | Witch-hazel | Astringent, analgesic, hematomas
Hypericum Perforatum | St. John’s wort | Neuropathic pains
Millefolium | Yarrow | Hematomas, wound healing
Symphytum Officinale | Comfrey | Neuropathy, causalgia,; contusions, periostitis
Zingiber Officinale | Ginger | Inflammation

INDICATIONS AND USAGE

Rapid Gel RX is indicated for the relief of pain and inflammation from: arthritis or injuries such as sprains, strains, dislocations, repetitive/overuse injuries, traumatic edema, post-surgical edema, general swelling of joints and soft tissues of the hand, wrist, elbow, shoulder, neck, back, knee, ankle, foot and toe and general aches and pains.

CONTRAINDICATIONS

Known sensitivity to Arnica Montana or any other ingredient.

PRECAUTIONS

Use in Pregnancy: No human or animal studies on the effect of Rapid Gel RX in pregnancy have been conducted.

Nursing Mothers: It is not known whether Rapid Gel RX is excreted in breast milk.

ADVERSE REACTIONS

Rarely, allergic skin reactions may occur. If allergic reactions occur, discontinue use of the drug.

DOSAGE AND ADMINISTRATION

Apply a thin layer (1 drop covers an area of skin 2 inches by 2 inches) to the affected area 3-4 times daily and rub in gently.

Applications of less than 3-4 times a day will not produce optimum results. Excess drops may be wiped from the area.

HOW SUPPLIED/STORAGE AND HANDLING

NDC 69176-070-30

HOMEOPATHIC TRANSDERMAL PAIN RELIEF GEL

RX ONLY NET CONTENTS 30g

NDC 69176-070-90

HOMEOPATHIC TRANSDERMAL PAIN RELIEF GEL

RX ONLY NET CONTENTS 90g

Manufactured for:

TMIG Inc.

Marietta, GA

WARNINGS

For external use only. Direct patient not to ingest Rapid Gel RX and to avoid contact with the eyes and mucous membranes, wounds, and damaged skin. If condition worsens, or if symptoms persist for more than seven days or clear up and occur again within a few days, patient should consult a doctor. If a rash develops, patient should discontinue use until rash clears. After the disappearance of rash, patient can try Rapid Gel RX again on a test area and monitor the site for additional results. If no rash or redness results, then patient can resume use. However, if the rash persists or redevelops, use should be discontinued.

Direct patient to keep this product out of reach of children and seek medical help or contact a Poison Control Center immediately if swallowed.